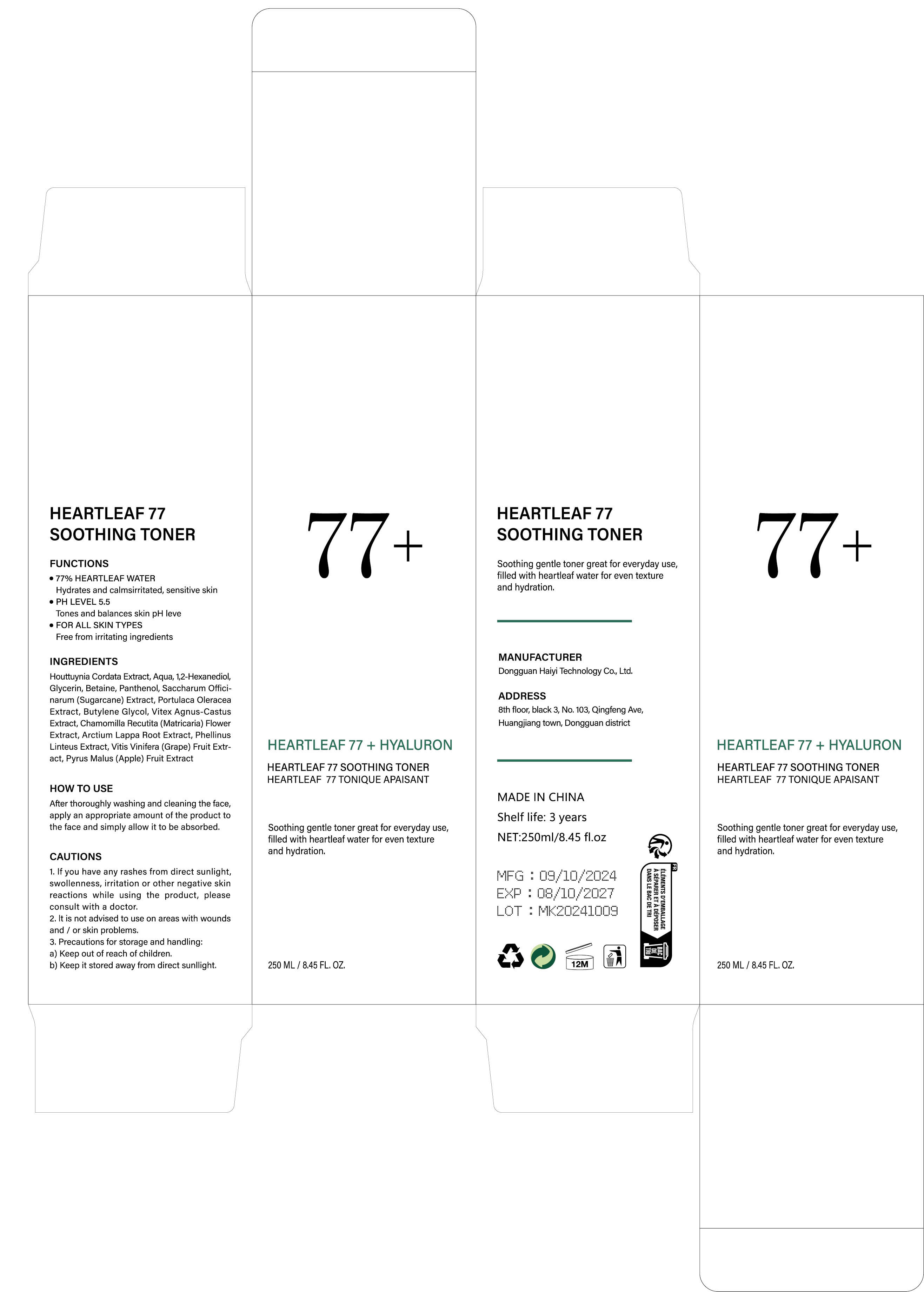 DRUG LABEL: 77 SOOTHING TONER
NDC: 84732-086 | Form: LIQUID
Manufacturer: Dongguan Haiyi Technology Co.,Ltd.
Category: otc | Type: HUMAN OTC DRUG LABEL
Date: 20241105

ACTIVE INGREDIENTS: GLYCERIN 7 mg/100 mL
INACTIVE INGREDIENTS: SUGARCANE; CHAMOMILE; PHELLINUS LINTEUS WHOLE; WINE GRAPE; APPLE; BETAINE; ARCTIUM LAPPA ROOT; WATER; PURSLANE; PANTHENOL; CHASTE TREE FRUIT; BUTYLENE GLYCOL; HOUTTUYNIA CORDATA EXTRACT; 1,2-HEXANEDIOL

Active ingredient

Glycerin

Inactive ingredient

Houttuynia Cordata Extract, Aqua, 1,2-Hexanediol, Betaine, Panthenol, Saccharum Officinarum (Sugarcane) Extract, Portulaca Oleracea Extract, Butylene Glycol, Vitex Agnus-CastusExtract, Chamomilla Recutita (Matricaria) Flower Extract, Arctium Lappa Root Extract, Phellinus Linteus Extract, Vitis Vinifera (Grape) Fruit Extract, Pyrus Malus (Apple) Fruit Extract

Purpose section

- 77% HEARTLEAF

WATERHydrates and calmsirritated, sensitive skin

- PH LEVEL 5.5

Tones and balances skin pH leve

- FOR ALL SKIN TYPES

Free from irritating ingredients

Warning

1. lf you have any rashes from direct sunlight,swollenness, irritation or other negative skinreactions while using the product, pleaseconsult with a doctor.

2. lt is not advised to use on areas with woundsand / or skin problems.

3. Precautions for storage and handling

:a) Keep out of reach of children.b) Keep it stored away from direct sunllight.

stop use

This product may cause allergic reactions in asmall number of people.
lf youexperience any discomfort,please stop using it immediately.

not use

Not suitable for use by children, pregnantor breast feeding people.

OUT OF CHILDREN

KEEP THE PRODUCT OUT OF REACH OF CHILDREN to

HOW TO USE

After thoroughly washing and cleaning the face,apply an appropriate amount of the product tothe face and simply allow it to be absorbed.

Dosage

take an appropriateamount,Use 2-3 times a week